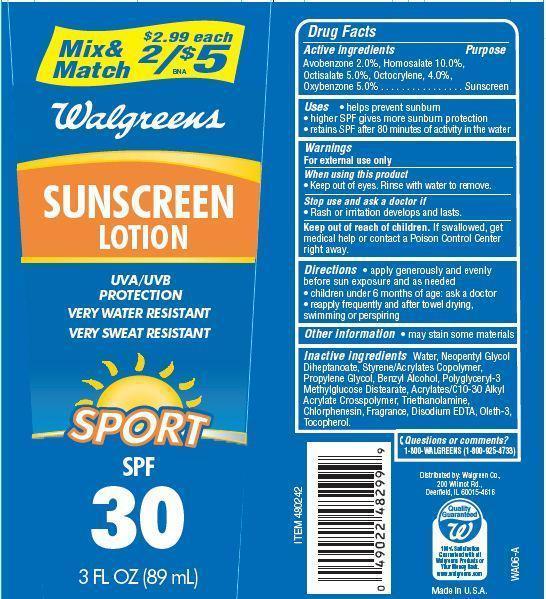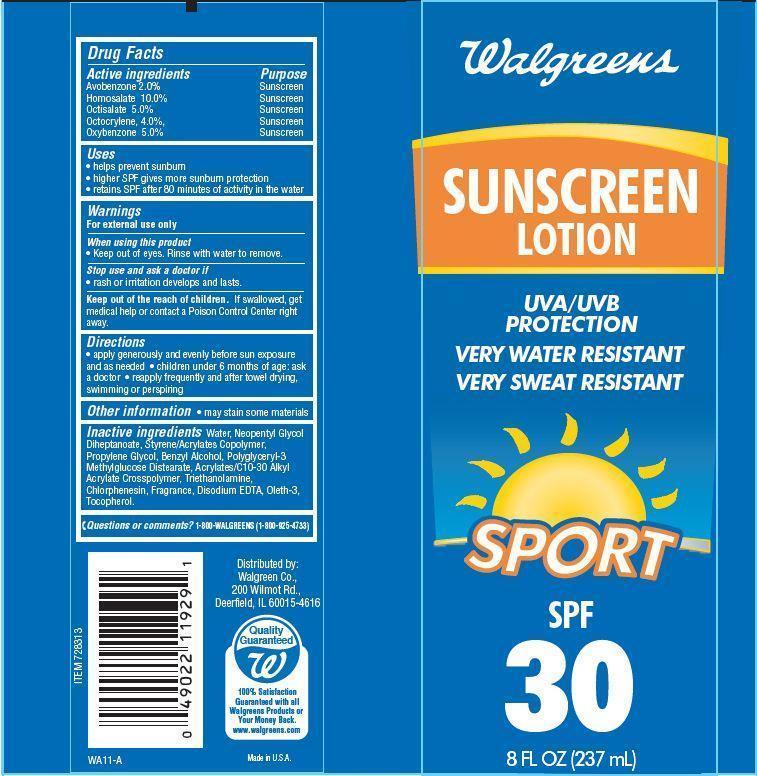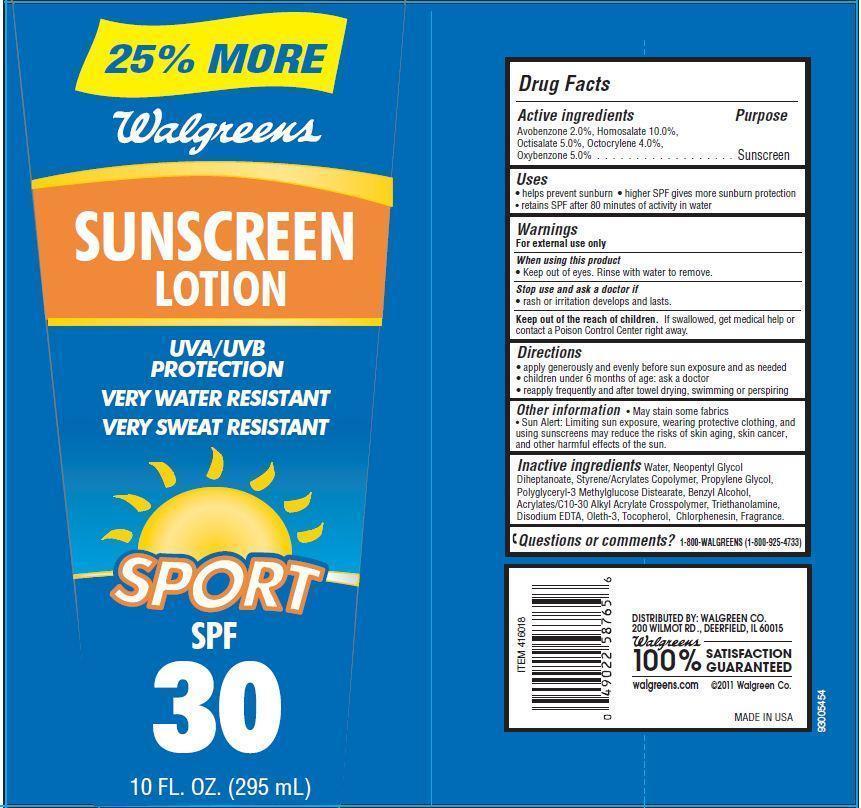 DRUG LABEL: Walgreens Sunscreen Sport
NDC: 0363-4005 | Form: LOTION
Manufacturer: WALGREEN CO.
Category: otc | Type: HUMAN OTC DRUG LABEL
Date: 20121204

ACTIVE INGREDIENTS: AVOBENZONE 2 g/100 g; HOMOSALATE 10 g/100 g; OCTISALATE 5 g/100 g; OCTOCRYLENE 4 g/100 g; OXYBENZONE 5 g/100 g
INACTIVE INGREDIENTS: WATER; NEOPENTYL GLYCOL DIHEPTANOATE; PROPYLENE GLYCOL; TROLAMINE; BENZYL ALCOHOL; CHLORPHENESIN; TOCOPHEROL; EDETATE DISODIUM

Drug Facts

Active ingredients

Avobenzone 2.0%
Homosalate 10.0%
Octisalate 5.0%
Octocrylene 4.0%
Oxybenzone 5.0%

Purpose

Sunscreen

Uses

- helps prevent sunburn
- higher SPF gives more sunburn protection
- retains SPF after 80 minutes of activity in the water

Warnings

For external use only

When using this product

- Keep out of eyes. Rinse with water to remove

Stop use and ask a doctor if

- rash or irritation develops and lasts.

Keep Out of the reach of children.

If swallowed get medical help or contact a Poison Control Center right away.

Directions

- apply generously and evenly before sun exposure and as needed
- children under 6 months of age:ask a doctor
- reapply frequently and after towel drying, swimming or perspiring.

Other Information

- May stain some fabrics
- Sun Alert: Limiting sun exposure, wearing protective clothing, and using sunscreens may reduce the risks of skin aging, skin cance, and other harmful effects of the sun.

Inactive ingredients

Water, Neopentyl Glycol Diheptanoate, Styrene/Acrylates Copolymer, Propylene Glycol, Polyglyceryl-3 Methylglucose Distearate, Benzyl Alcohol, Acrylates/C10-30 Alkyl Acrylate Crosspolymer, Triethanolamine, Disodium EDTA, Oleth-3, Tocopherol, Chlorphenesin, Fragrance.

Principal Display Panel

25% MORE
Walgreens
SUNSCREEN
LOTION
UVA/UVB
PROTECTION
VERY WATER RESISTANT
VERY SWEAT RESISTANT
SPORT
SPF
30
10 FL.OZ. (295 mL)
Mix and Match $2.99 each
2/$5
Walgreens
SUNSCREEN
LOTION
UVA/UVB
PROTECTION
VERY WATER RESISTANT
VERY SWEAT RESISTANT
SPORT
SPF
30
3 FL.OZ. (89 mL)
Walgreens
SUNSCREEN
LOTION
UVA/UVB
PROTECTION
VERY WATER RESISTANT
VERY SWEAT RESISTANT
SPORT
SPF
30
8 FL.OZ. (237 mL)